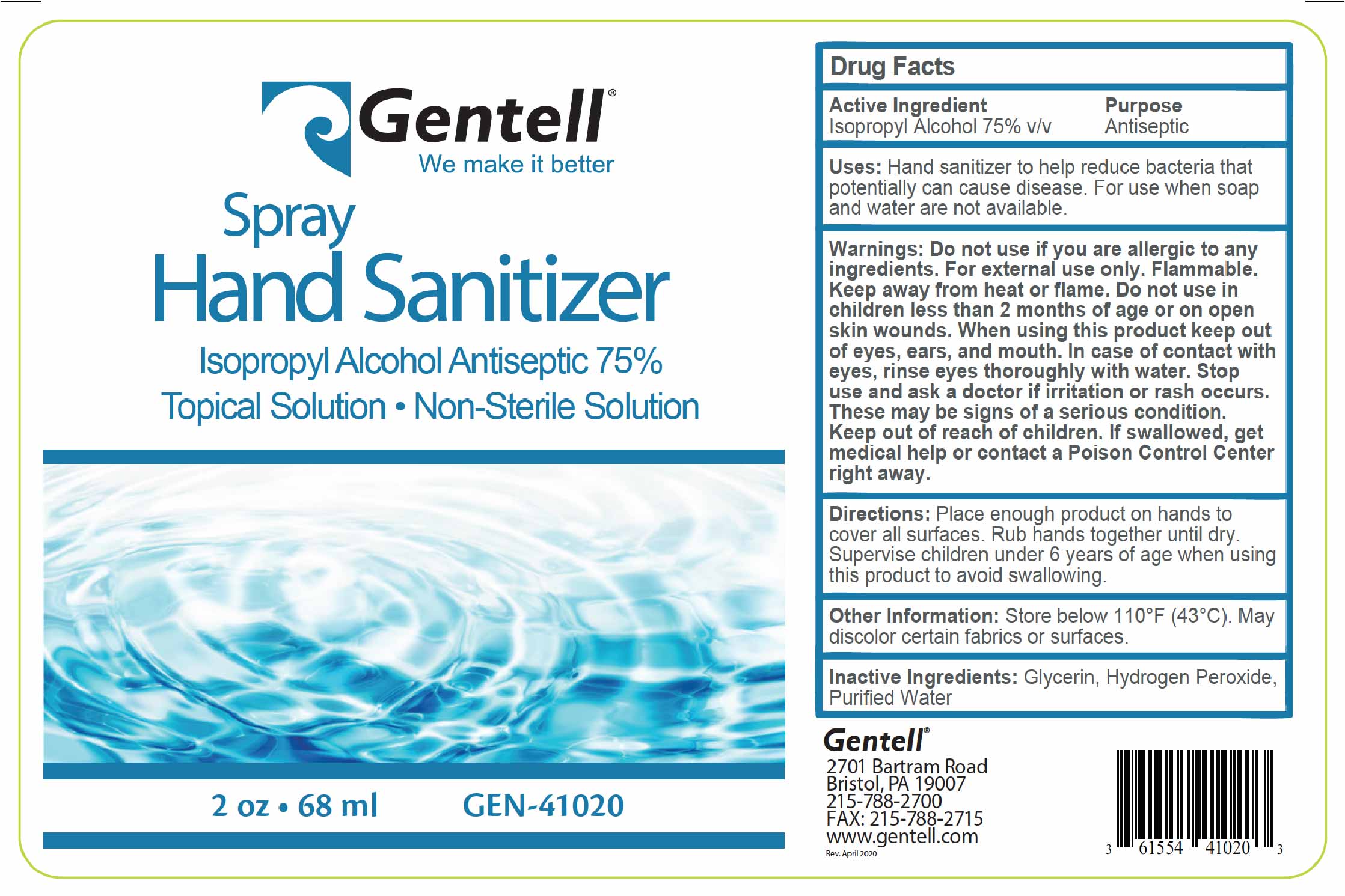 DRUG LABEL: Hand Sanitizer
NDC: 61554-410 | Form: AEROSOL, SPRAY
Manufacturer: Gentell
Category: otc | Type: HUMAN OTC DRUG LABEL
Date: 20200609

ACTIVE INGREDIENTS: ISOPROPYL ALCOHOL 75 mL/100 mL
INACTIVE INGREDIENTS: GLYCERIN 1.45 mL/100 mL; HYDROGEN PEROXIDE 0.125 mL/100 mL; WATER

Spray Hand Sanitizer

Active Ingredient(s)

Isopropyl Alcohol 75% v/v. Purpose: Antiseptic

Purpose

Antiseptic

Use

Hand Sanitizer to help reduce bacteria that potentially can cause disease. For use when soap and water are not available.

Warnings

Do not use if you are allergic to any ingredients. For external use only. Flammable. Keep away from heat or flame

Do not use

in children less than 2 months of age or on open skin wounds

When using this product keep out of eyes, ears, and mouth. In case of contact with eyes, rinse eyes thoroughly with water.
Stop use and ask a doctor if irritation or rash occurs. These may be signs of a serious condition.
Keep out of reach of children. If swallowed, get medical help or contact a Poison Control Center right away.

Stop use and ask a doctor if irritation or rash occurs. These may be signs of a serious condition.

Keep out of reach of children. If swallowed, get medical help or contact a Poison Control Center right away.

Directions

- Place enough product on hands to cover all surfaces. Rub hands together until dry.
- Supervise children under 6 years of age when using this product to avoid swallowing.

Other information

- Store between 15-30C (59-86F)
- Avoid freezing and excessive heat above 40C (104F)

Inactive ingredients

glycerin, hydrogen peroxide, purified water USP

Package Label - Principal Display Panel

Gentell We make it better

Spray Hand Sanitizer

Isopropyl Alcohol Antiseptic 75%

Topical Solution

Non-Sterile Solution

2 oz 68 mL

GEN-41020

Gentell

2701 Bartram Road

Bristol, PA 19007

215-788-2700

FAX: 215-788-2715

www.gentell.com

Rev. April 2020